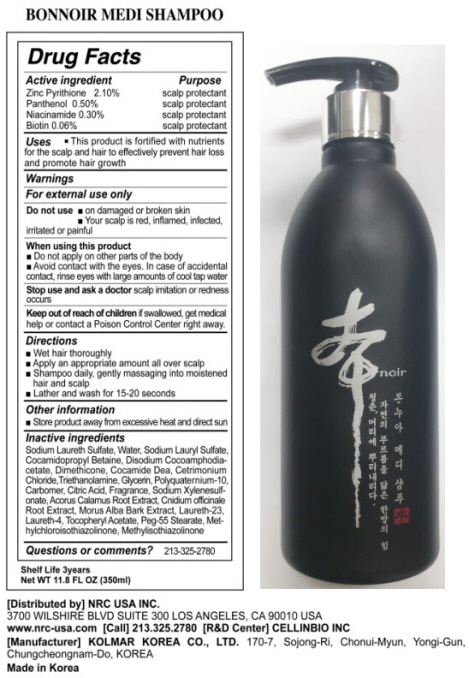 DRUG LABEL: BONNOIR HAIR MEDI
NDC: 76173-1002 | Form: SHAMPOO
Manufacturer: Cellinbio Co Ltd
Category: otc | Type: HUMAN OTC DRUG LABEL
Date: 20110727

ACTIVE INGREDIENTS: PYRITHIONE ZINC 7.35 mL/350 mL; PANTHENOL 1.75 mL/350 mL; NIACINAMIDE 1.05 mL/350 mL; BIOTIN 0.21 mL/350 mL
INACTIVE INGREDIENTS: SODIUM LAURETH SULFATE; WATER; SODIUM LAURYL SULFATE; COCAMIDOPROPYL BETAINE; DISODIUM COCOAMPHODIACETATE; DIMETHICONE; COCO DIETHANOLAMIDE; CETRIMONIUM CHLORIDE; TROLAMINE; GLYCERIN; POLYQUATERNIUM-10 (400 CPS AT 2%); CARBOMER 934; CITRIC ACID MONOHYDRATE; SODIUM XYLENESULFONATE; ACORUS CALAMUS ROOT; CNIDIUM OFFICINALE ROOT; MORUS ALBA BARK; LAURETH-23; LAURETH-4; .ALPHA.-TOCOPHEROL ACETATE, D-; PEG-12 STEARATE; METHYLCHLOROISOTHIAZOLINONE; METHYLISOTHIAZOLINONE

Bonnoir Hair Medi Shampoo

Drug Facts

Active ingredient
Zinc Pyrithione 2.10%
Panthenol 0.50%
Niacinamide 0.30%
Biotin 0.06%

Purpose

Scalp protectant

Keep out of reach of children if swallowed, get medical help or contact a Poison Control Center right away.

Indication & Usage

Directions
Wet hair thoroughly
Apply an appropriate amount all over scalp
Shampoo daily, gently massaging into moisten hair and scalp
Lather and wash for 15-20 seconds

Warnings

For extenal use only

Do not use on damaged or broken skin. Your scalp is red, inflamed, infected, irritated or painful

When using this product
Do not apply on other parts of the body
Avoid contact with the eyes. In case of accidental contact, rinse eyes with large amounts of cool tap water

Dosage & Administration

Uses
This product is fortified with nutrients for the scalp and hair to effectively prevent hair loss and promote hair growth

Inactive Ingredient

Sodium Laureth Sulfate, Water, Sodium Lauryl Sulfate, Cocamidopropyl Betaine, Disodium Cocoamphodiacetate, Dimethicone, Cocamide Dea, Cetrimonium Chloride, Triethanolamine, Glycerin, Polyquaternium-10, Carbomer, Citric Acid, Fragrance, Sodium Xylenesulfonate, Acorus Calamus Root Extract, Cnidium officinale Root Extract, Morus Alba Bark Extract, Laureth-23, Laureth-4, Tocopheryl Acetate, Peg-55 Stearate, Methylchloroisothiazolinone, Methylisothiazolinone

Bonnoir Hair Medi Shampoo

NRC Bonnoir Hair Medi Shampoo

Net WT. 11.8 FL OZ(350ml)